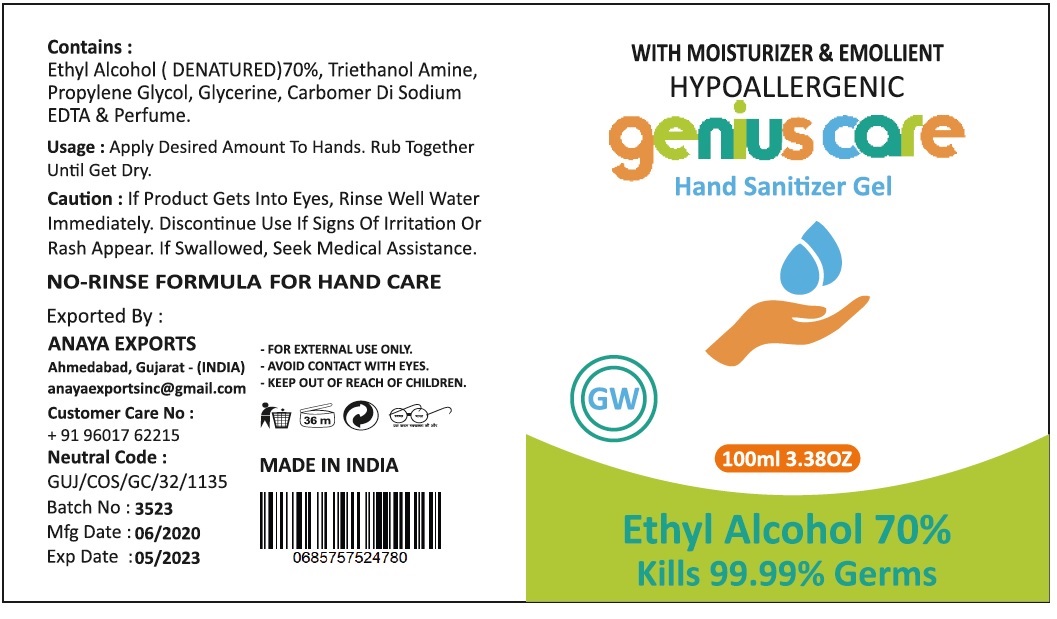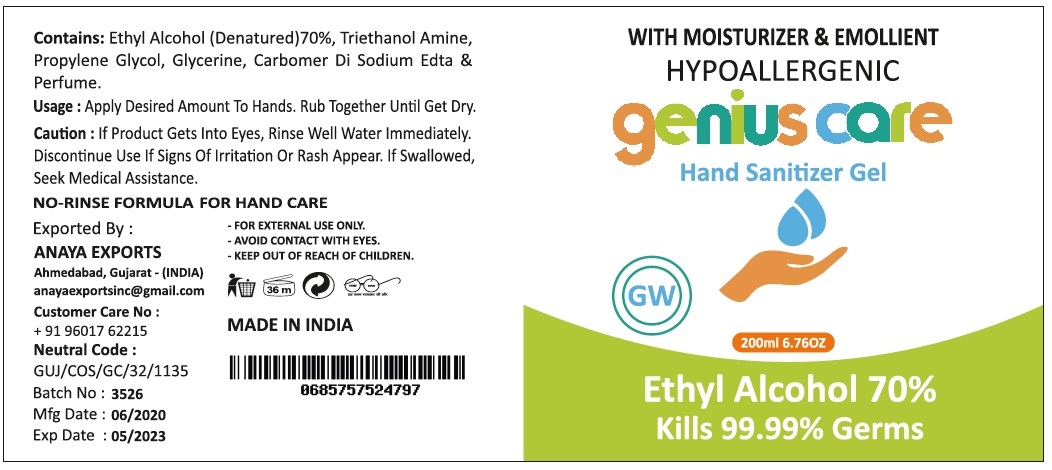 DRUG LABEL: Genius Care Hand Sanitizer
NDC: 90102-312 | Form: GEL
Manufacturer: Gokul Wholesale, Inc.
Category: otc | Type: HUMAN OTC DRUG LABEL
Date: 20200810

ACTIVE INGREDIENTS: ALCOHOL 70 mL/100 mL
INACTIVE INGREDIENTS: TROLAMINE; PROPYLENE GLYCOL; GLYCERIN; CARBOMER HOMOPOLYMER, UNSPECIFIED TYPE; EDETATE DISODIUM ANHYDROUS

genius care Hand Sanitizer Gel

Active Ingredient: Ethyl Alcohol (Denatured)70%

Purpose: Antiseptic

INDICATIONS AND USAGE

Use: Hand Sanitizer To Decrease Bacteria On The Skin

WARNINGS

Caution: If Product Gets Into Eyes, Rinse Well Water Immediately. Discontinue Use If Signs Of Irritation Or Rash Appear. If Swallowed, Seek Medical Assistance.

NO-RINSE FORMULA FOR HAND CARE

- FOR EXTERNAL USE ONLY.

- AVOID CONTACT WITH EYES

- KEEP OUT OF REACH OF CHILDREN

DOSAGE AND ADMINISTRATION

Usage: Apply Desired Amount To Hands. Rub Together Until Get Dry.

INACTIVE INGREDIENT

Contains: Ethyl Alcohol (Denatured)70%, Triethanol Amine, Propylene Glycol, Glycerine, Carbomer Di Sodium Edta & Perfume.

WITH MOISTURIZER & EMOLLIENT

HYPOALLERGENIC

GW

Kills 99.99% Germs

Exported By:

ANAYA EXPORTS

Ahmedabad, Gujarat - (INDIA)

anayaexportsinc@gmail.com

Customer Care No: + 91 96017 62215

Neutral Code: GUJ/COS/GC/32/1135

MADE IN INDIA